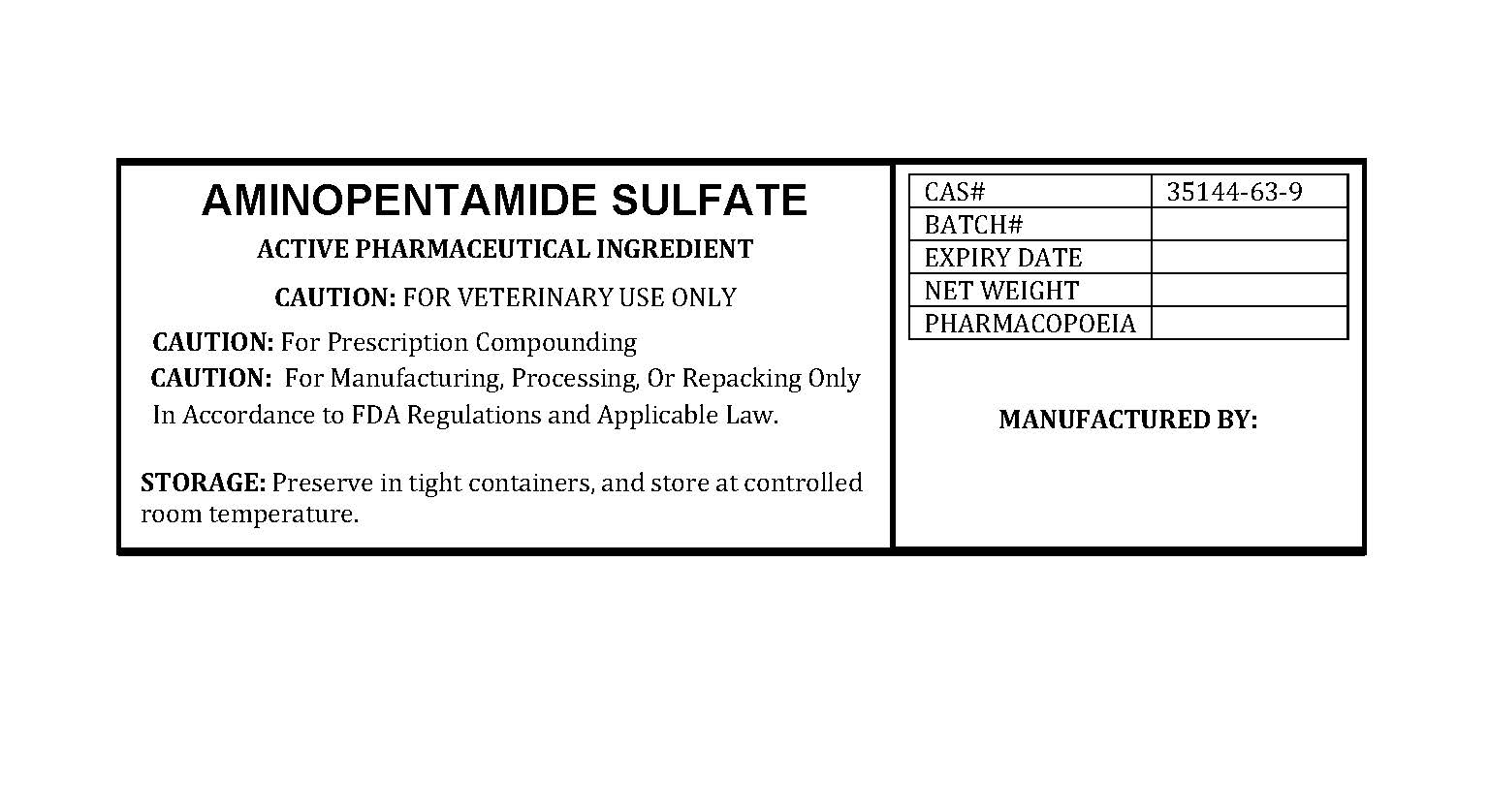 DRUG LABEL: AMINOPENTAMIDE SULFATE
NDC: 86184-004 | Form: POWDER
Manufacturer: MAEDA INC
Category: other | Type: BULK INGREDIENT - ANIMAL DRUG
Date: 20250923

ACTIVE INGREDIENTS: AMINOPENTAMIDE SULFATE 1 g/1 g

AMINOPENTAMIDE SULFATE

PACKAGE LABEL

aminopentamidesulfatelabelfile.jpg